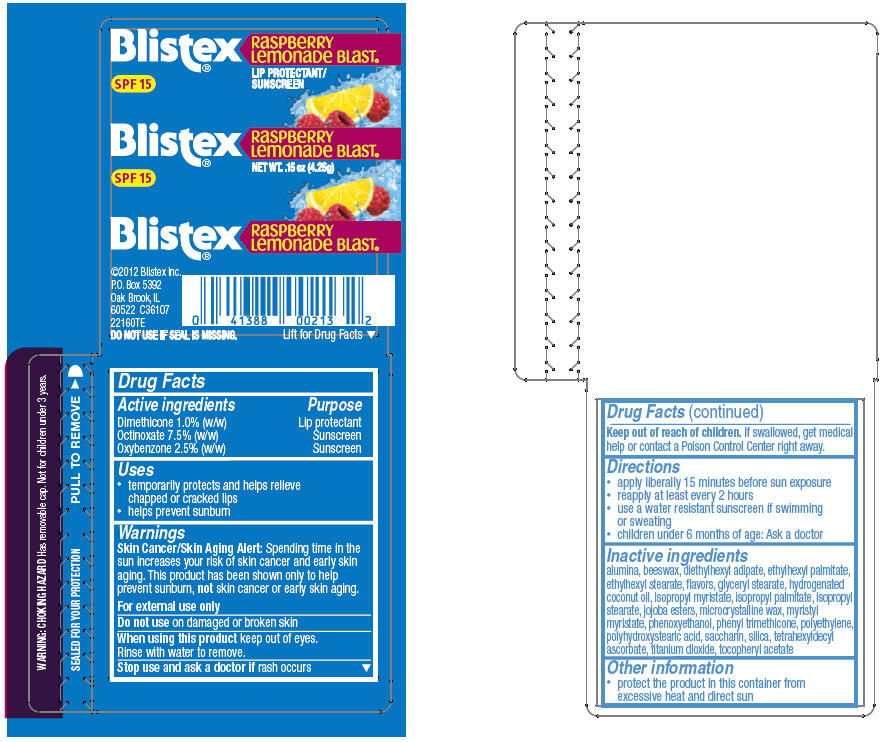 DRUG LABEL: Blistex 
NDC: 10157-9800 | Form: STICK
Manufacturer: Blistex Inc
Category: otc | Type: HUMAN OTC DRUG LABEL
Date: 20130312

ACTIVE INGREDIENTS: Dimethicone 1 g/100 g; Octinoxate 7.5 g/100 g; Oxybenzone 2.5 g/100 g
INACTIVE INGREDIENTS: aluminum oxide; yellow wax; diethylhexyl adipate; ethylhexyl palmitate; ethylhexyl stearate; glyceryl monostearate; hydrogenated coconut oil; isopropyl myristate; isopropyl palmitate; isopropyl stearate; microcrystalline wax; myristyl myristate; phenoxyethanol; phenyl trimethicone; high density polyethylene; saccharin; silicon dioxide; tetrahexyldecyl ascorbate; titanium dioxide; .alpha.-tocopherol acetate

Blistex®
Raspberry Lemonade Blast®

Drug Facts

ACTIVE INGREDIENT

Active ingredients | Purpose
Dimethicone 1.0% (w/w) | Lip protectant
Octinoxate 7.5% (w/w) | Sunscreen
Oxybenzone 2.5% (w/w) | Sunscreen

Uses

- temporarily protects and helps relieve chapped or cracked lips
- helps prevent sunburn

Warnings

Skin Cancer/Skin Aging Alert

Spending time in the sun increases your risk of skin cancer and early skin aging. This product has been shown only to help prevent sunburn, not skin cancer or early skin aging.

For external use only

Do not use on damaged or broken skin

When using this product keep out of eyes.

Rinse with water to remove.

Stop use and ask a doctor if rash occurs

Keep out of reach of children. If swallowed, get medical help or contact a Poison Control Center right away.

Directions

- apply liberally 15 minutes before sun exposure
- reapply at least every 2 hours
- use a water resistant sunscreen if swimming or sweating
- children under 6 months of age: Ask a doctor

Inactive ingredients

alumina, beeswax, diethylhexyl adipate, ethylhexyl palmitate, ethylhexyl stearate, flavors, glyceryl stearate, hydrogenated coconut oil, isopropyl myristate, isopropyl palmitate, isopropyl stearate, jojoba esters, microcrystalline wax, myristyl myristate, phenoxyethanol, phenyl trimethicone, polyethylene, polyhydroxystearic acid, saccharin, silica, tetrahexyldecyl ascorbate, titanium dioxide, tocopheryl acetate

Other information

- protect the product in this container from excessive heat and direct sun

PRINCIPAL DISPLAY PANEL - 4.25 g Cylinder Label

Blistex®

SPF 15

RaSPBeRRY
LemonaDe BLaST®

NET WT. .15 oz (4.25g)